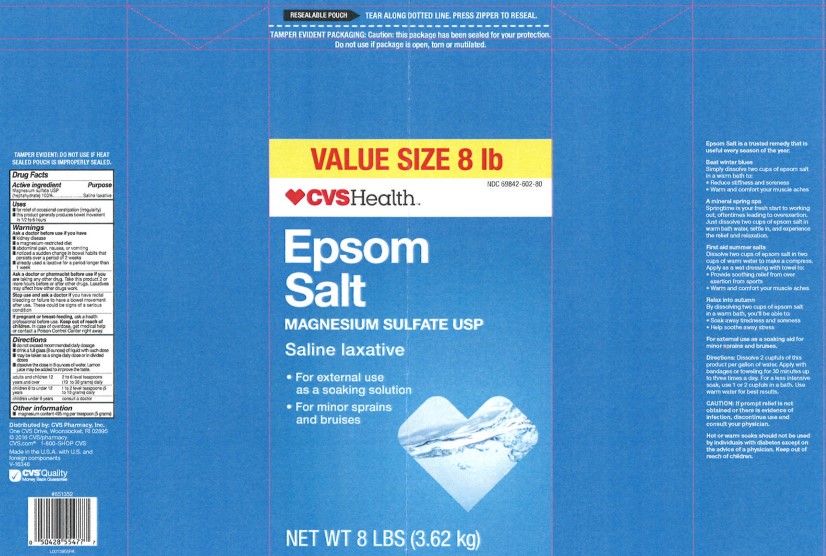 DRUG LABEL: Epsom Salt
NDC: 69842-602 | Form: GRANULE, FOR SOLUTION
Manufacturer: CVS Pharmacy, Inc.
Category: otc | Type: HUMAN OTC DRUG LABEL
Date: 20260203

ACTIVE INGREDIENTS: MAGNESIUM SULFATE HEPTAHYDRATE 1 g/1 g

CVS 602.002/602AA
Epsom Salt

Tamper Evident Statement

TAMPER EVIDENT: DO NOT USE IF HEAT SEALED POUCH IS IMPROPERLY SEALED.

Active ingredient

Magnesium sulfate USP (Heptahydrate) 100%

Purpose

Saline laxative

Uses

- for relief of occasional constipation (irregularity)
- this product generally produces bowel movement in 1/2 to 6 hours

Warnings

for this product

Ask a doctor before use if you have

- kidney disease
- a magnesium-restricted diet
- abdominal pain, nausea or vomiting
- noticed a sudden change in bowel habits that persists over a period of 2 weeks
- already used a laxative for a period longer than 1 week

Ask a doctor or pharmacist before use if you are

taking any other drug. Take this product 2 or more hours before or after other drugs. Laxatives may affect how other drugs work.

Stop use and ask a doctor if

you have rectal bleeding or failure to have a bowel movement after use. These could be signs of a serious condition.

If pregnant or breast-feeding,

ask a health professional before use.

Keep out of reach of children.

In case of overdose, get medical help or contact a Poison Control Center right away.

Directions

- do not exceed recommended daily dosage
- drink a full glass (8 ounces) of liquid with each dose
- may be taken as a single daily dose or in divided doses
- dissolve the dose in 8 ounces of water. Lemon juice may be added to improve the taste

adults and children 12 years and over - 2 to 6 level teaspoons (10 to 30 grams) daily

children 6 to under 12 years - 1 to 2 level teaspoons (5 to 10 grams) daily

children under 6 years - consult a doctor

Other information

- magnesium content 495 mg per teaspoon (5 grams)

Inactive Ingredient

None

ADVERSE REACTION

Epsom Salt is a trusted remedy that is useful every season of the year.

Beat winter blues

Simply dissolve two cups of epsom salt in a warm bath to:
• Reduce stiffness and soreness
• Warm and comfort your muscle aches

A mineral spring spa

Springtime is your fresh start to working out, often times leading to overexertion. Just dissolve two cups of epsom salt in warm bath water, settle in, and experience the relief and relaxation.

First aid summer salts
Dissolve two cups of epsom salt in two cups of hot water to make a compress.
Apply as a wet dressing with towel to:
• Provide soothing relief from over exertion from sports
• Warm and comfort your muscle aches

Relax into autumn
By dissolving two cups of epsom salt in a warm bath, you'll be able to:
• Soak away tiredness and soreness
• Help soothe away stress

For external use as a soaking aid for minor sprains and bruises.

Directions: Dissolve 2 cupfuls of this product per gallon of water. Apply with bandages or toweling for 30 minutes up to three times a day. For a less intensive soak, use 1 or 2 cupfuls in a bath. Use warm water for best results.

CAUTION: If prompt relief is not obtained or there is evidence of infection, discontinue use and consult your physician.
Hot or warm soaks should not be used by individuals with diabetes except on the advice of a physician. Keep out of reach of children.

Distributed by: CVS Pharmacy, Inc.
One CVS Drive, Woonsocket, RI 02895
© 2016 CVS/pharmacy
CVS.com®1-800-SHOP CVS
Made in the U.S.A. with U.S. and foreign components

CVS®Quality

Money Back Guarantee

principal display panel

RESEALABLE POUCH

TEAR ALONG DOTTED LINE. PRESS ZIPPER TO RESEAL.

TAMPER EVIDENT PACKAGING: Caution: this package has been sealed for your protection.

Do not use if package is open, torn or mutilated.

Value Size 8 lb

NDC 69842-602-80

CVS Health™

Epsom Salt

Magnesium Sulfate USP

Saline Laxative

- For external use as a soaking solution
- For minor sprains and bruises

NET WT 8 LBS (3.62 kg)